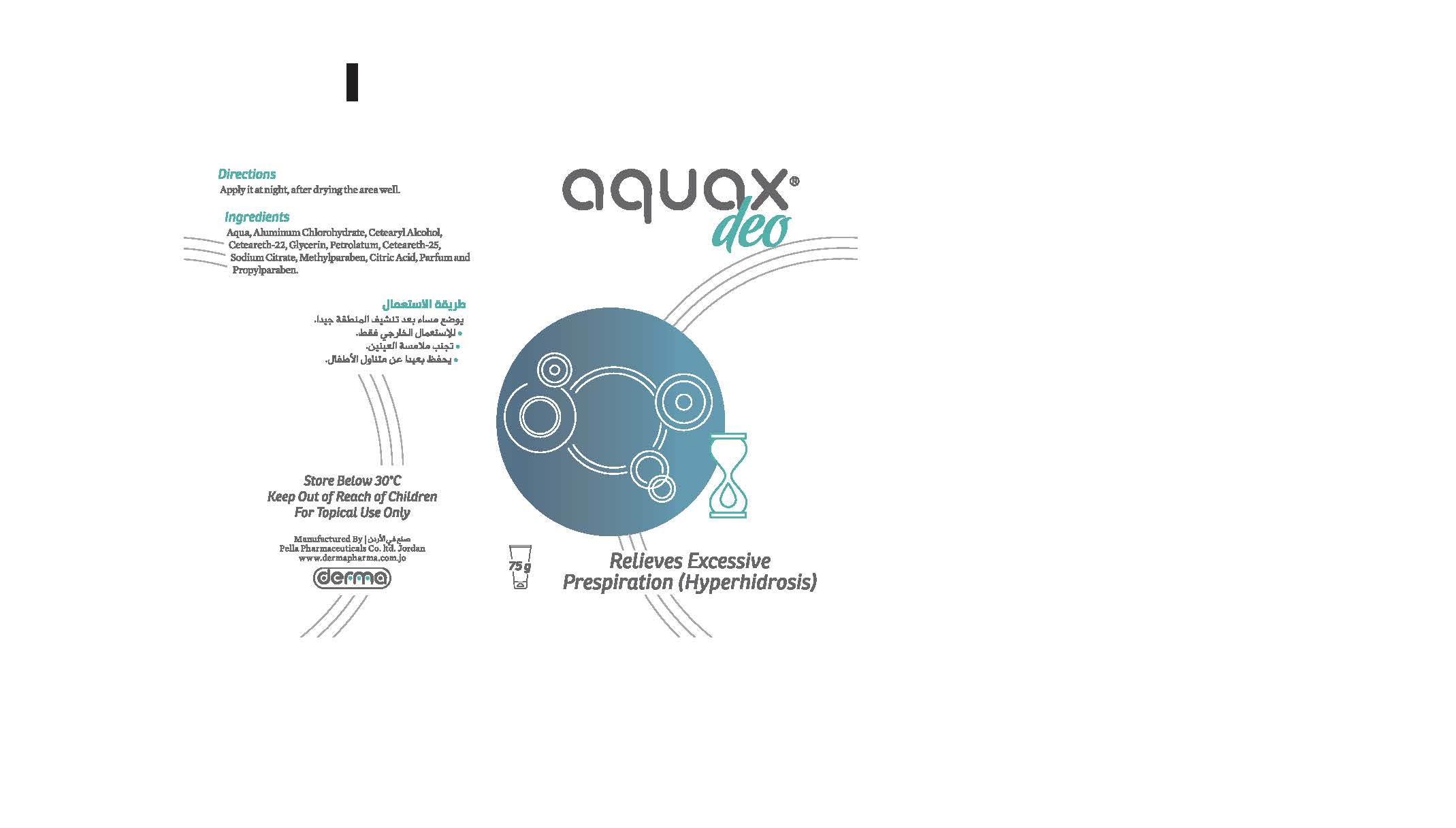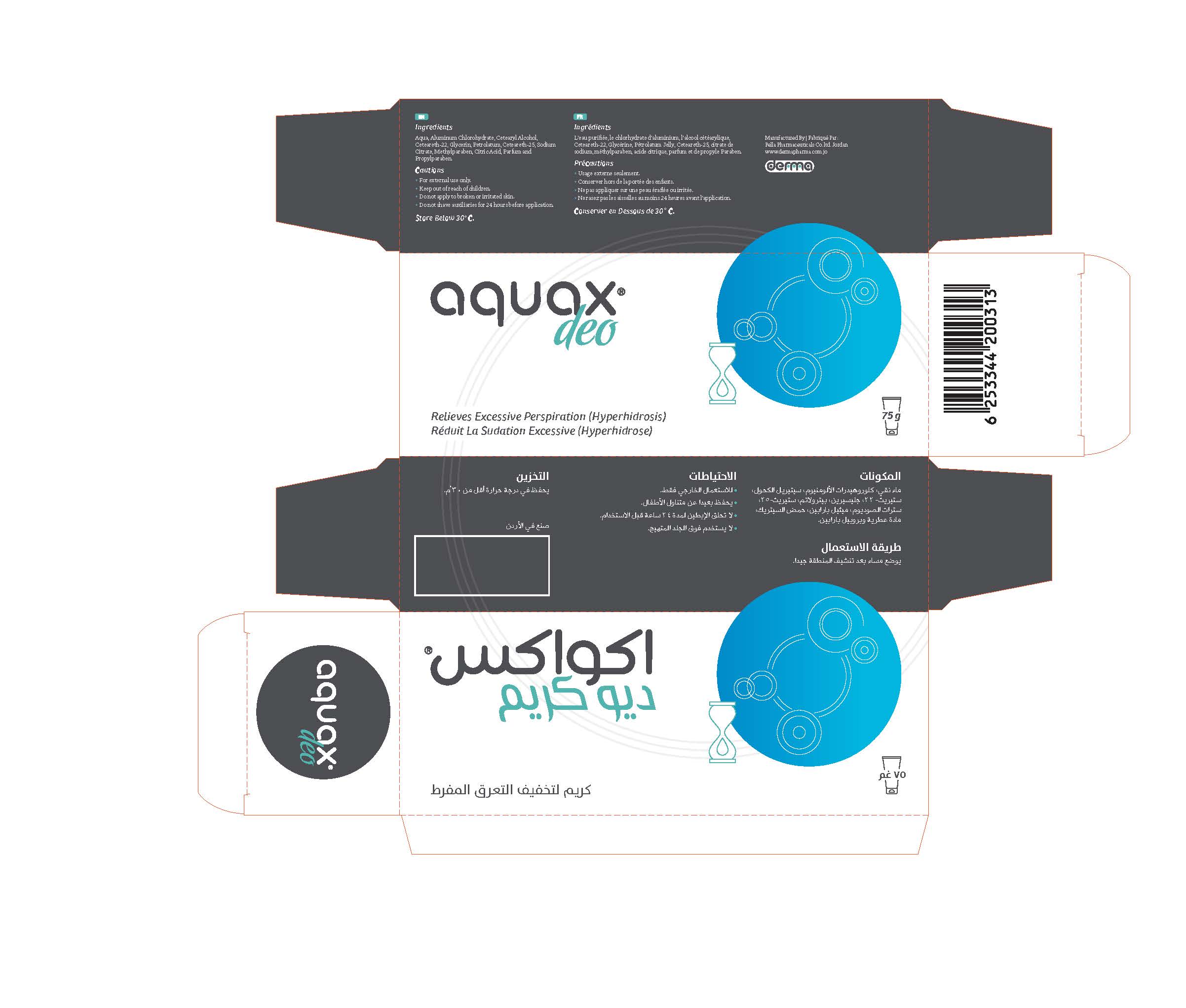 DRUG LABEL: Aquax Deo
NDC: 82160-313 | Form: CREAM
Manufacturer: Pella Pharmaceuticals Co. Ltd
Category: otc | Type: HUMAN OTC DRUG LABEL
Date: 20211125

ACTIVE INGREDIENTS: ALUMINUM CHLOROHYDRATE 150 mg/75 g
INACTIVE INGREDIENTS: WATER; ANHYDROUS CITRIC ACID; CETEARETH-22; CETOSTEARYL ALCOHOL; PETROLATUM; CETEARETH-25; SODIUM CITRATE; METHYLPARABEN; PROPYLPARABEN; GLYCERIN

Deo

Forms and presentation

Cream: Tube of 75 g

Active Ingredient

Aluminum Chlorohydrate

Inactive Ingredients

Aqua, Cetearyl Alcohol, Ceteareth-22, Glycerin, Petrolatum, Ceteareth-25, Sodium Citrate, Methylparaben, Citric Acid, Parfum, Propylparaben.

Purpose

Antiperspirant

Properties

Aquax® Deo cream reduces excessive sweating (hyperhidrosis)

Indications

Aquax® Deo cream is used to reduce excessive perspiraton (hyperhidrosis)

Precautions

keep out of reach of children

Warnings

- For external use only
- Do not apply to broken or irritated skin
- Do not shave auxiliaries for 24 hours before application

Contraindications

Hypersensitivity to any of the components

Side effects

Aquax® Deo cream has no known side effect, its us is without risk

Dosage and administration

Dry the area to be treated, and then apply Aquax® Deo cream at night, at bed time

Storage conditions

Store at a temperature belwo 30 °C